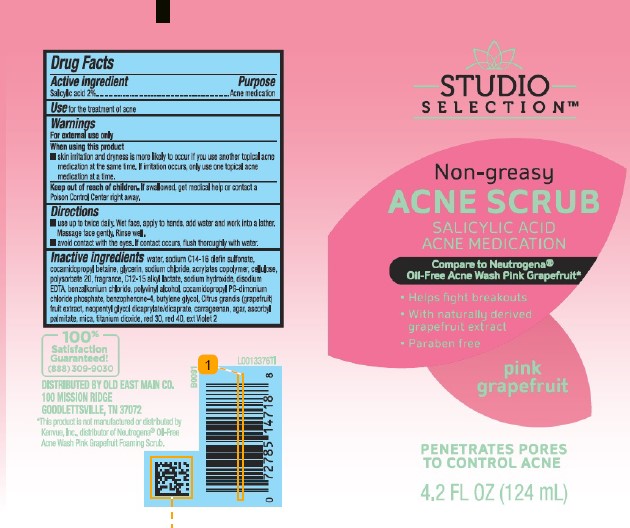 DRUG LABEL: Acne Scrub
NDC: 55910-821 | Form: GEL
Manufacturer: Old East Main Co.
Category: otc | Type: HUMAN OTC DRUG LABEL
Date: 20260302

ACTIVE INGREDIENTS: SALICYLIC ACID 21 mg/1 mL
INACTIVE INGREDIENTS: WATER; SODIUM C14-16 OLEFIN SULFONATE; COCAMIDOPROPYL BETAINE; GLYCERIN; SODIUM CHLORIDE; BUTYL ACRYLATE/METHYL METHACRYLATE/METHACRYLIC ACID COPOLYMER (18000 MW); MICROCRYSTALLINE CELLULOSE; POLYSORBATE 20; C12-15 ALKYL LACTATE; SODIUM HYDROXIDE; EDETATE DISODIUM; BENZALKONIUM CHLORIDE; POLYVINYL ALCOHOL, UNSPECIFIED; COCAMIDOPROPYL PROPYLENE GLYCOL-DIMONIUM CHLORIDE PHOSPHATE; SULISOBENZONE; BUTYLENE GLYCOL; PUMMELO; NEOPENTYL GLYCOL DICAPRYLATE/DICAPRATE; CARRAGEENAN; AGAR, UNSPECIFIED; ASCORBYL PALMITATE; MICA; TITANIUM DIOXIDE; D&C RED NO. 30; FD&C RED NO. 40; D&C VIOLET NO. 2

Studio Selections 821.004/821AH
Acne Scrub Pink Grapefruit

Active ingredient

Salicylic acid 2%

Purpose

Acne Medication

use

For the treatment of acne

Warnings

For external use only

When using this product

- skin irritation and dryness is more likely to occur if you use another topical acne medication at the same time. If irritation occurs, only use one topical acne medication at a time.

Keep out of reach of children.

If swallowed, get medical help or contact a Poison Control Center right away.

Directions

- use up to twice daily. Wet face, apply to hands, add water and work into a lather. Massage face gently. Rinse well.
- avoid contact with the eyes. If contact occurs, flush thoroughly with water.

Inactive ingredients

water, sodium C14-16 olefin sulfonate, cocamidopropyl betaine, glycerin, sodium chloride, acrylates copolymer, cellulose, polysorbate 20, fragrance, C12-15 alkyl lactate, sodium hydroxide, disodium EDTA, benzalkonium chloride, polyvinyl alcohol, cocamidopropyl PG-dimonium chloride phosphate, benzophenone-4, butylene glycol, Citrus grandis (grapefruit) fruit extract, neopentyl glycol dicaprylate/dicaprate, carrageenan, agar, ascorbyl palmitate, mica, titanium dioxide, red 30, red 40, ext Violet 2

Adverse reactions

100% Satisfaction Guaranteed!

(888)309-9030

DISTRIBUTED BY Old East Main CO.

100 MISSION RIDGE

GOODLETTSVILLE, TN 37072

Disclaimer

*This product is not manufactured or distributed by Kenvue, Inc., distributed of Neutrogena® Oil-Free Acne Wash Pink Grapefruit Foaming Scrub.

Principal display panel

STUDIO SELECTION™

Non-greasy

ACNE SCRUB

SALICYLIC ACID

ACNE MEDICATION

Compare to Neutrogena® Oil-Free Acne Wash Pink Grapefruit*

- Helps fight breakouts
- With naturally derived grapefruit extract
- Paraben free

pink grapefruit

PENETRATES PORES TO CONTROL ACNE

4.2 fl oz (124 mL)